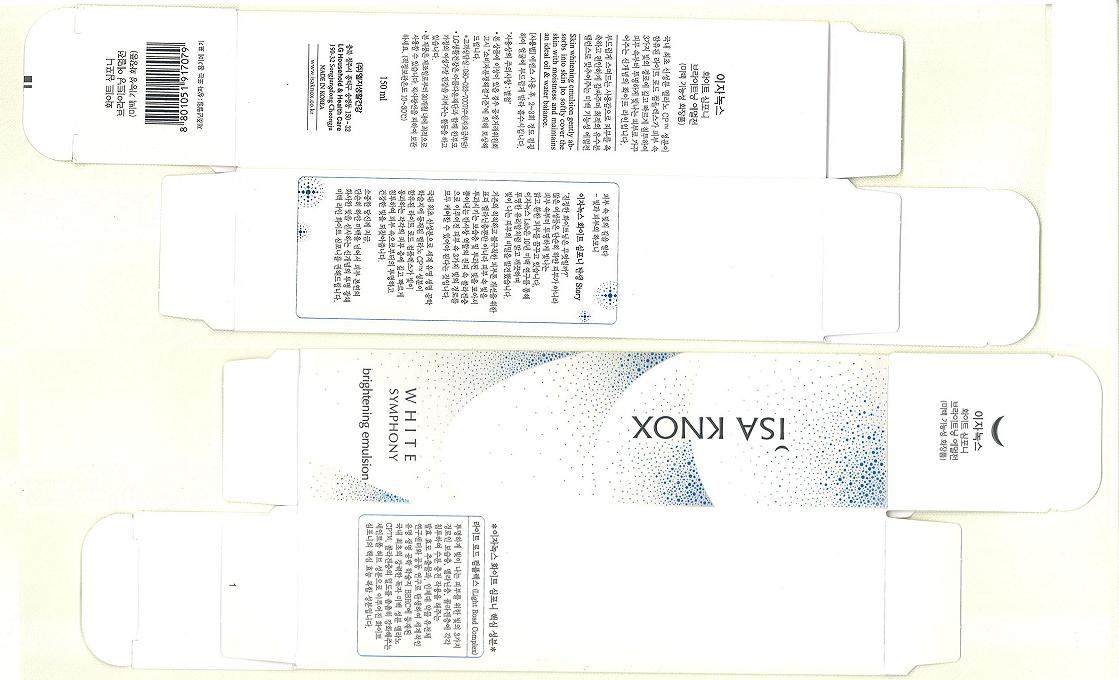 DRUG LABEL: ISAKNOX WHITE SYMPHONY BRIGHTENING EMULSION
NDC: 53208-385 | Form: LOTION
Manufacturer: LG Household and Healthcare, Inc.
Category: otc | Type: HUMAN OTC DRUG LABEL
Date: 20100329

ACTIVE INGREDIENTS: ARBUTIN 2.1 g/100 g
INACTIVE INGREDIENTS: WATER; GLYCERIN; ALCOHOL; CAPRIC ACID; GLYCERYL MONOSTEARATE; CETOSTEARYL ALCOHOL; SILICON DIOXIDE; POLYETHYLENE GLYCOL; 2-ETHYLHEXANOIC ACID; DIMETHICONE; GLYCERYL MONOSTEARATE; METHYLPARABEN; BETAINE; TROLAMINE; PROPYLPARABEN; ETHYLPARABEN; DIPROPYLENE GLYCOL; CARBOMER 934; EDETATE TRISODIUM
; FD&C YELLOW NO. 6; FD&C YELLOW NO. 5

Drug Facts

ACTIVE INGREDIENT

ARBUTIN 2.10g/100g

WARNINGS AND PRECAUTIONS

For external use only

Keep out of reach of children. Is swallowed, get medical help or contact a Poison Control Center right away.

WHEN USING

Keep out of eyes. Rinse with water to remove.

Stop use if a rash or irritation develops and lasts.